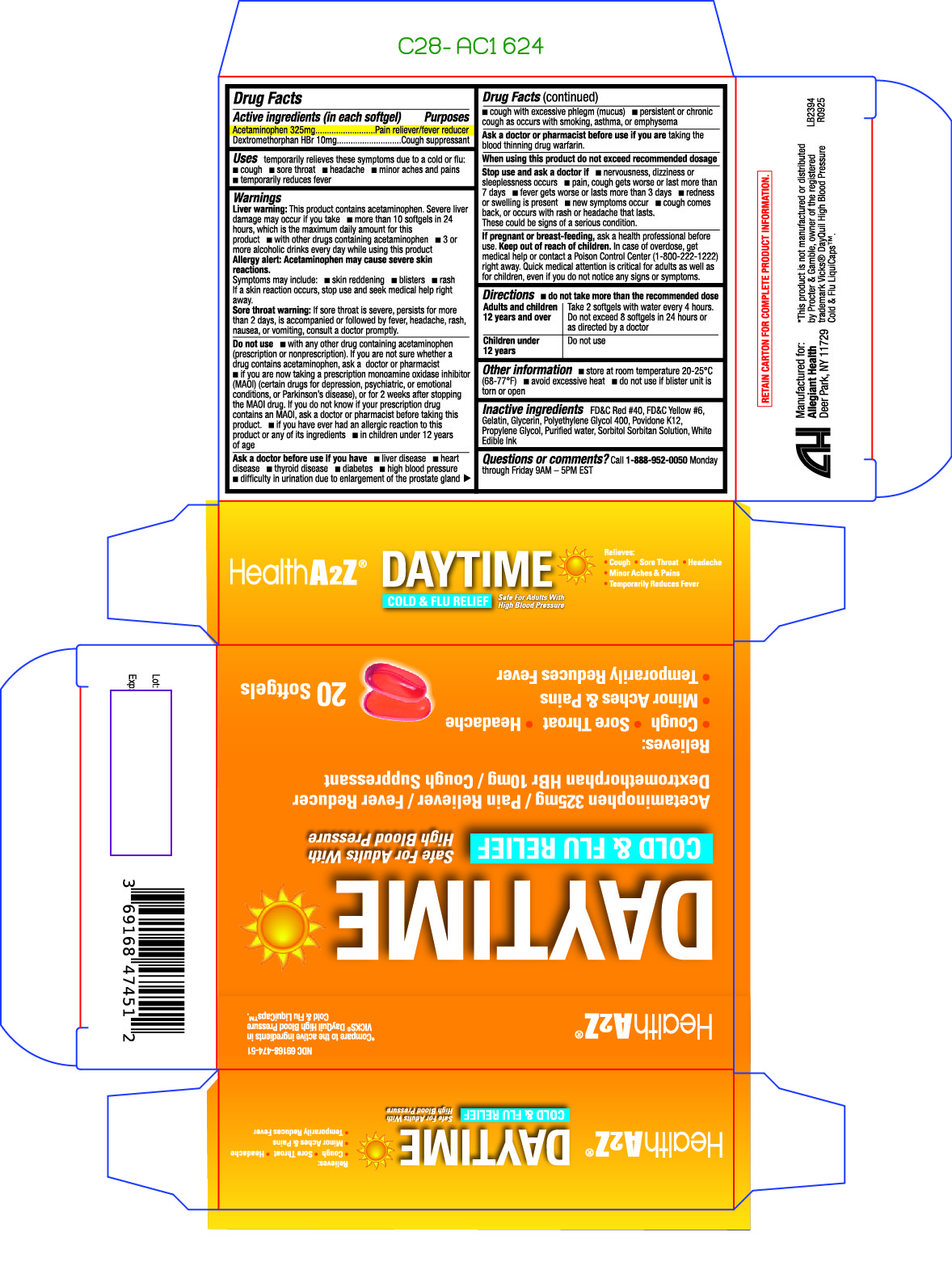 DRUG LABEL: Daytime Cold and Flu
NDC: 69168-474 | Form: CAPSULE, LIQUID FILLED
Manufacturer: Allegiant Health
Category: otc | Type: HUMAN OTC DRUG LABEL
Date: 20260109

ACTIVE INGREDIENTS: ACETAMINOPHEN 325 mg/1 1; DEXTROMETHORPHAN HYDROBROMIDE 10 mg/1 1
INACTIVE INGREDIENTS: FD&C RED NO. 40; FD&C YELLOW NO. 6; GELATIN; GLYCERIN; POLYETHYLENE GLYCOL 400; POVIDONE K12; PROPYLENE GLYCOL; WATER; SORBITOL

474 - Daytime Cold and Flu Relief

Active ingredient(s)

Acetaminophen 325mg

Dextromethorphan HBr 10mg

Purpose

Pain reliever/fever reducer
Cough suppressant

Use(s)

temporarily relieves these symptoms due to cold flu:

- cough
- sore throat
- headache
- minor aches and pains
- temporarily reduces fever

Warnings

Liver warning: This product contains acetaminophen. Severe liver damage may occur if you take:
• more than 10 softgels in 24 hours, which is the maximum daily amount for this product
• with other drugs containing acetaminophen
• 3 or more alcoholic drinks every day while using this product

Sore throat warning: If sore throat is severe, persists for more than 2 days, is accompanied or followed by fever, headache, rash, nausea, or vomiting, consult a doctor promptly.

Allergy alert: Acetaminophen may cause severe skin reactions. Symptoms may include:
• skin reddening
• blisters
• rash
If a skin reaction occurs, stop use and seek medical help right away.

Do not use if you have

- with any other drug containing acetaminophen (prescription or nonprescription). If you are not sure whether a drug contains acetaminophen, ask a doctor or pharmacist.
- if you are now taking a prescription monoamine oxidase inhibitor (MAOI) (certain drugs for depression, psychiatric, or emotional conditions, or Parkinson's disease), or for 2 weeks after stopping the MAOI drug. If you do not know if your prescription drug contains an MAOI, ask a doctor or pharmacist before taking this product.
- if you have ever had an allergic reaction to this product or any of its ingredients
- in children under 12 years of age

Ask a doctor before use if you

- liver disease
- heart disease
- high blood pressure
- thyroid disease
- diabetes
- cough with excessive phlegm (mucus)
- difficulty in urination due to enlargement of the prostate gland
- persistent or chronic cough such as occurs with smoking, asthma, or emphysema

Ask a doctor or pharmacist before use if

if you are taking the blood thinning drug warfarin.

When using this product

do not exceed recommended dosage.

Stop use and ask a doctor if

• pain, cough gets worse or lasts more than 7 days
• fever gets worse or lasts more than 3 days
• redness or swelling is present
• new symptoms occur
• cough comes back or occurs with rash or headache that lasts. These could be signs of a serious condition.
• nervousness, dizziness, or sleeplessness occurs

If pregnant or breastfeeding,

ask a health professional before use.

Keep out of reach of children

In case of overdose, get medical help or contact a Poison Control Center (1-800-222-1222)
right away. Quick medical attention is critical for adults as well as
for children, even if you do not notice any signs or symptoms.

Directions

- do not take more than the recommended dose
  Adults and children 12 years and over: Take 2 softgels with water every 4 hours. Do not exceed 8 softgels in 24 hours or as directed by a doctor

Children under 12 years: Do not use

Other information

- store at room temperature 20-25°C (68-77°F)
- avoid excessive heat
- do not use if blister unit is torn or open

Inactive ingredients

FD&C Red #40, FD&C Yellow #6, Gelatin, Glycerin, Polyethylene Glycol 400, Povidone K12,
Propylene Glycol, Purified water, Sorbitol Sorbitan Solution, White Edible Ink

Questions/Comments

Call 1-888-952-0050

(Monday-Friday 9 AM – 5 PM EST)

Principal Display Panel

Daytime Cold and Flu